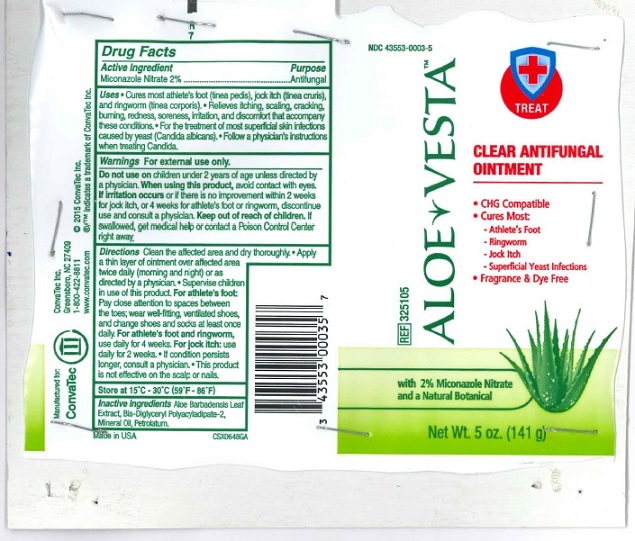 DRUG LABEL: Aloe Vesta Clear Antifungal 141g
NDC: 11099-0006 | Form: OINTMENT
Manufacturer: Guest Packaging LLC.
Category: otc | Type: HUMAN OTC DRUG LABEL
Date: 20160619

ACTIVE INGREDIENTS: MICONAZOLE NITRATE 2.82 g/141 g
INACTIVE INGREDIENTS: ALOE VERA LEAF; BIS-DIGLYCERYL POLYACYLADIPATE-2; MINERAL OIL; PETROLATUM

Aloe Vesta TM Clear Antifungal Ointment 141g

Uses

- Cures most athlete's foot (tinea pedis), jock itch (tinea cruris), and ringworm (tinea corporis).
- Relieves itching, scaling, cracking, burning, redness, soreness, irritation, and discomfort that accompany these conditions.
- For treatment of most superficial skin infections caused by yeast (Candida albicans).
- Follow a physician's instructions when treating Candida.

Warnings

For external use only.
Do not use on children under 2 years of age unless directed by a physician.
When using this product, avoid contact with eyes. If irritation occurs or if there is no improvement within 2 weeks for jock itch, or 4 weeks for athlete's foot or ringworm, discontinue use and consult a physician.

Keep out of reach of children. If swallowed, get medical help or consult a Poison Control Center right away.

Directions

Clean the affected area and dry thoroughly.

- Apply a thin layer of ointment over affected area twice daily (morning and night) or as directed by a physician.
- Supervise children in use of this product.

For athlete's foot: Pay close attention to spaces between the toes; wear well-fitting, ventilated shoes, and change shoes and socks at least once daily.

For athlete's foot and ringworm, use daily for 4 weeks.

For jock itch: use daily for 2 weeks

- If condition persists longer, consult a physician.
- This product is not effective on the scalp or nails.

Active ingredient

Miconazole Nitrate 2%

Purpose

Antifungal

Inactive ingredients

Aloe Barbadensis Leaf Extract, Bis-Diglyceryl Polyacladipate-2, Mineral Oil, Petrolatum

STORAGE AND HANDLING

Store at 15°C -30°C (59°F - 86°F)

CLEAR ANTIFUNGALOINTMENT

- CHG Compatible
- Cures Most:

-Athlete's Foot
-Ringworm
-Jock Itch
-Superficial Yeast Infections

- Fragrance & Dye Free

with 2 % Miconazole Nitrate and a Natural Botanical

Manufactured for:
ConvaTec
ConvaTec Inc.
Greensboro, NC 27409
1-800-422-8811
www.convatec.com

Made in USA